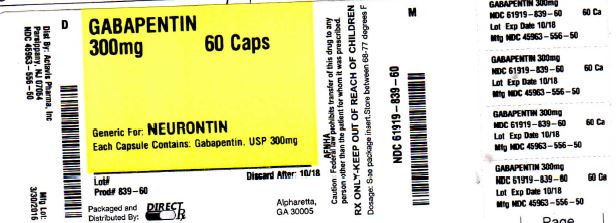 DRUG LABEL: GABAPENTIN
NDC: 61919-839 | Form: CAPSULE
Manufacturer: DIRECT RX
Category: prescription | Type: HUMAN PRESCRIPTION DRUG LABEL
Date: 20160331

ACTIVE INGREDIENTS: GABAPENTIN 300 mg/1 1
INACTIVE INGREDIENTS: MANNITOL; FERRIC OXIDE RED; SILICON DIOXIDE; TALC; TITANIUM DIOXIDE; FERRIC OXIDE YELLOW; SHELLAC; D&C YELLOW NO. 10; FD&C BLUE NO. 1; FD&C RED NO. 40; GELATIN; SODIUM LAURYL SULFATE; FERROSOFERRIC OXIDE; FD&C BLUE NO. 2; PROPYLENE GLYCOL; STARCH, CORN

GABAPENTIN 300mg